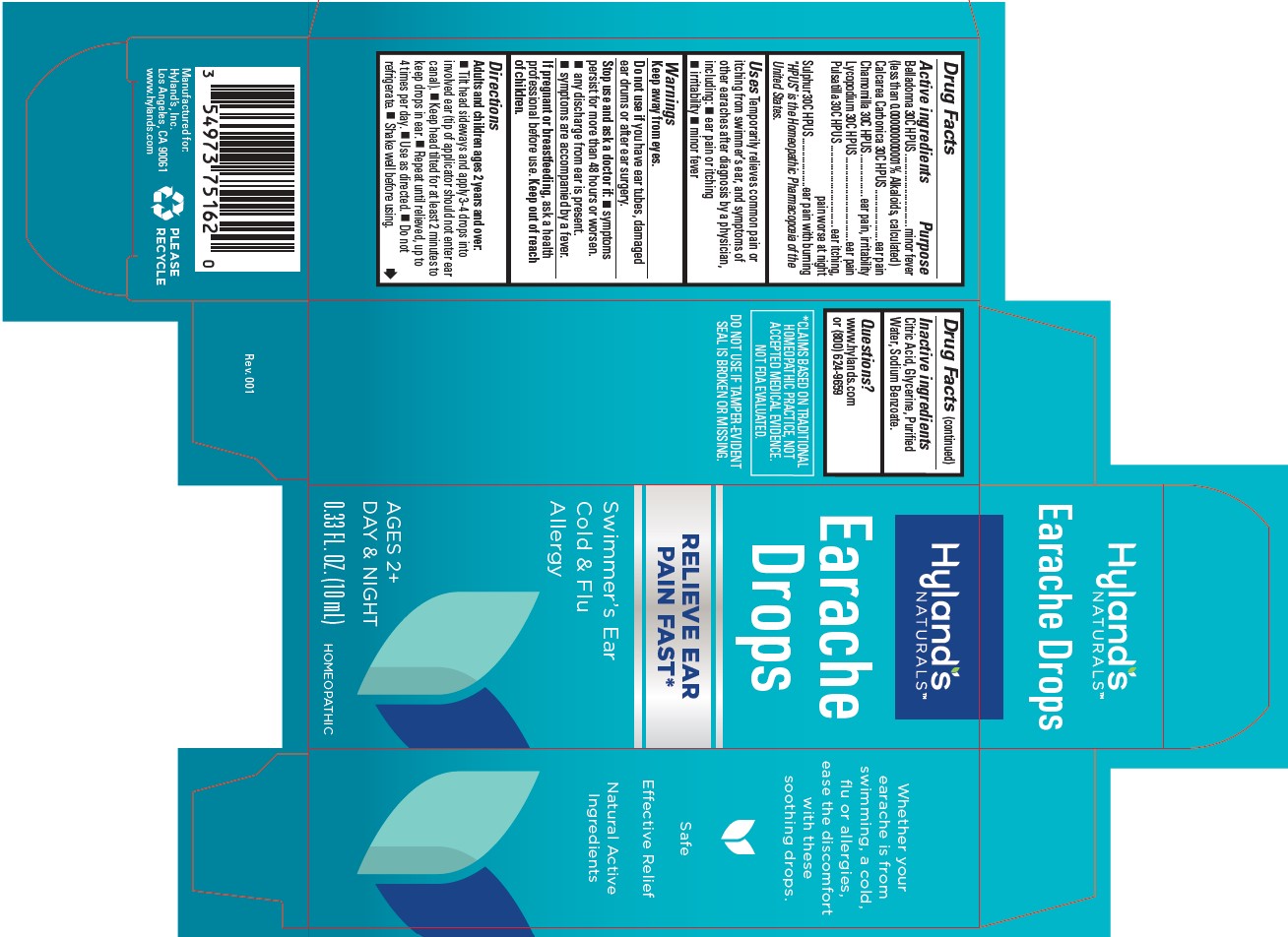 DRUG LABEL: EARACHE DROPS
NDC: 54973-3172 | Form: LIQUID
Manufacturer: Hyland's Inc.
Category: homeopathic | Type: HUMAN OTC DRUG LABEL
Date: 20221212

ACTIVE INGREDIENTS: BELLADONNA LEAF 30 [hp_C]/1 mL; CALCIUM CARBONATE 30 [hp_C]/1 mL; CHAMOMILE 30 [hp_C]/1 mL; LYCOPODIUM CLAVATUM SPORE 30 [hp_C]/1 mL; ANEMONE PATENS WHOLE 30 [hp_C]/1 mL; SULFUR 30 [hp_C]/1 mL
INACTIVE INGREDIENTS: CITRIC ACID MONOHYDRATE; WATER; SODIUM BENZOATE; GLYCERIN

Hyland's Naturals Earache Drops

Purpose

Temporarily relieves common pain or itching from swimmer’s ear, and symptoms of other earaches after diagnosis by a physician, including: ear pain or itching, irritability, minor fever

Drug Facts

Active ingredients | Purpose
Belladonna 30C HPUS; (less than 0.000000000001% Alkaloids, calculated) | minor fever
Calcarea Carbonica 30C HPUS | throbbing ear pain
Chamomilla 30C HPUS | occasional sleeplessness and irritability
Lycopodium 30C HPUS | ear pain
Pulsatilla 30C HPUS | ear itching, pain worse at night
Sulphur 30C HPUS | ear pain with burning

"HPUS" indicates that the active ingredients are in the official Homeopathic Pharmacopœia of the United States.

Uses

Temporarily relieves common pain or itching from swimmer’s ear, and symptoms of other earaches after diagnosis by a physician,
including: ■ ear pain or itching ■ irritability ■ minor fever

Warnings

Keep away from eyes.

Do not use

you have ear tubes, damaged ear drums or after ear surgery.

Stop use and ask a doctor if:

■ symptoms persist for more than 48 hours or worsen.
■ any discharge from ear is present.
■ symptoms are accompanied by a fever.

If pregnant or breastfeeding

ask a health professional before use.

Directions

Adults and children ages 2 years and over: ■ Tilt head sideways and apply 3-4 drops into involved ear (tip of applicator should not enter ear canal). ■ Keep head tilted for at least 2 minutes to keep drops in ear. ■ Repeat until relieved, up to 4 times per day. ■ Use as directed. ■ Do not refrigerate. ■ Shake well before using.

Drug Facts (continued)

Inactive ingredients

Citric Acid, Glycerine, Purified Water, Sodium Benzoate.

Questions?

www.hylands.com or (800) 624-9659

Indications and Usage

Uses Temporarily relieves the symptoms of: 

- minor fever 
- ear pain or throbbing 
- irritability or occasional sleeplessness associated with earaches after diagnosis by a physician 
- common pain or itching of "swimmer’s ear"

Temporarily relieves common pain or itching from swimmer’s ear, and other earache symptoms after diagnosis by a physician, including:  ear pain, throbbing or itching  irritability  occasional sleeplessness  minor fever

Dosage and Administration (Dirctions)

■ Shake well before using. Adults and children ages 2 years and over: Tilt head sideways and apply 3-4 drops into involved ear (tip
of applicator should not enter ear canal). Keep head tilted for at least 2 minutes to keep drops in ear. Repeat until relieved, up to 4 times daily.

PRINCIPAL DISPLAY PANEL

Hyland's

NATURALS

Earache

Drops

RELIEVE EAR

PAIN FAST*

Swimmer's Ear

Cold & Flu

Allergy

AGES 2+

DAY & NIGHT

0.33 FL. OZ. (10 mL)

HOMEOPATHIC